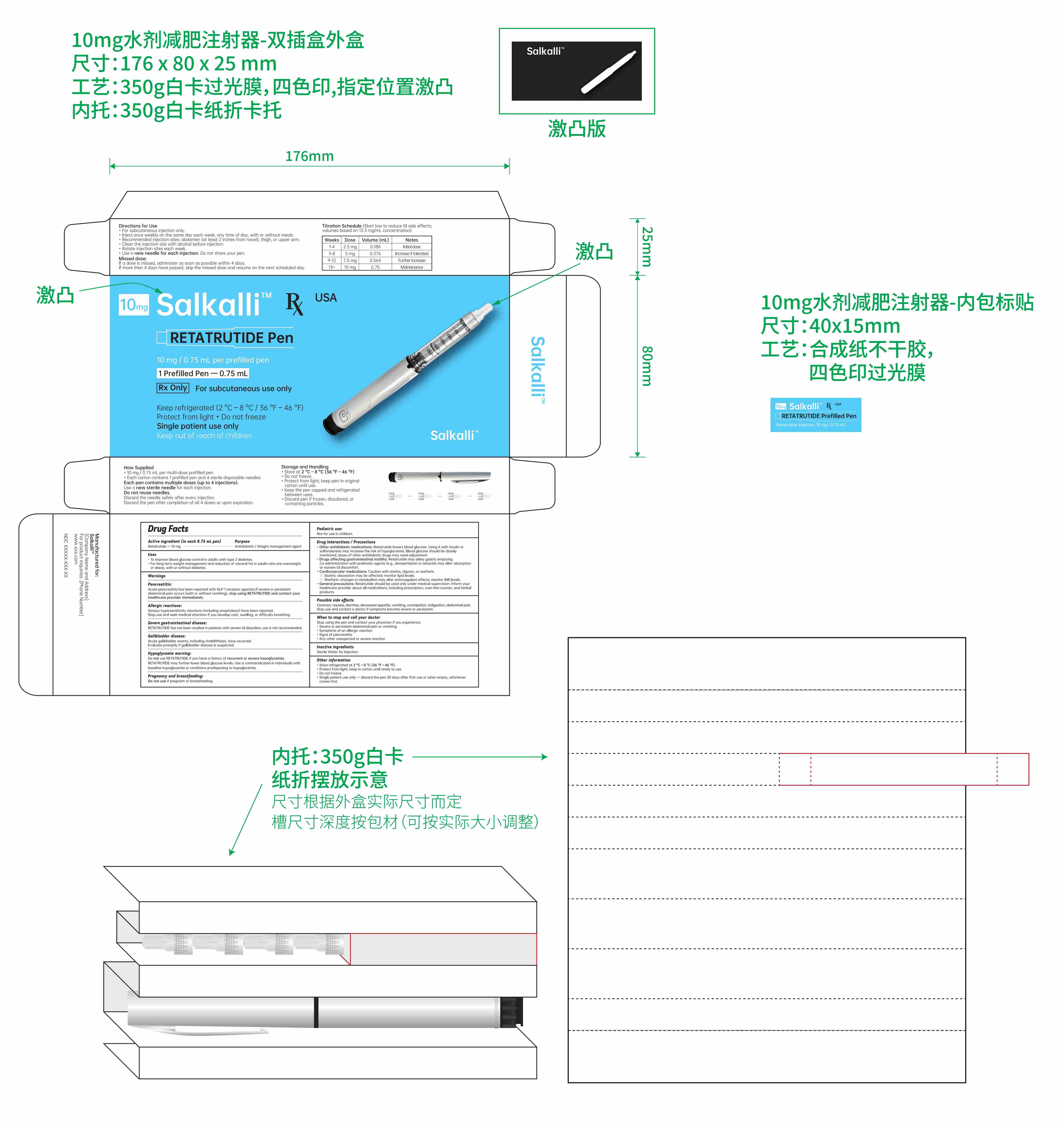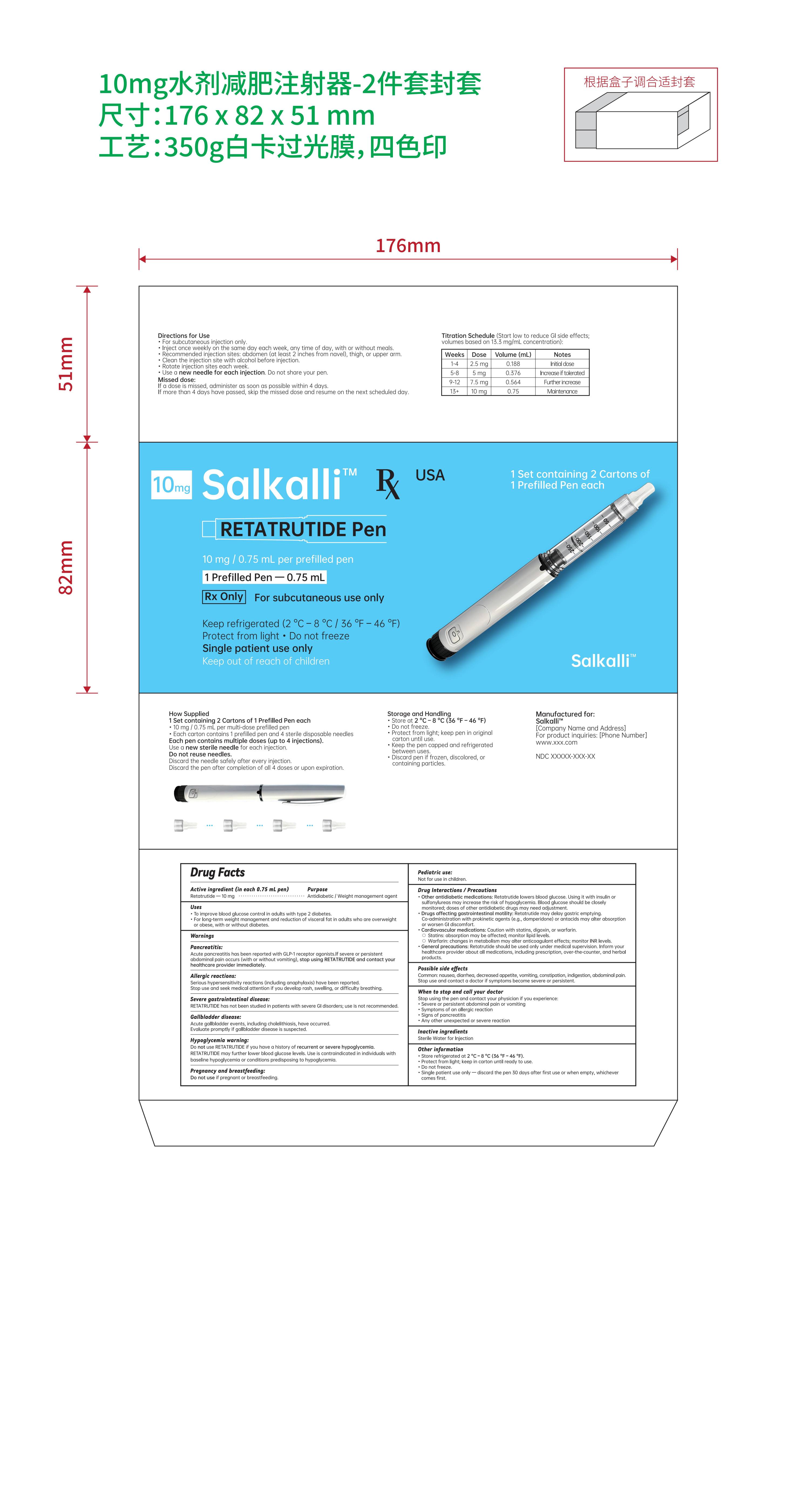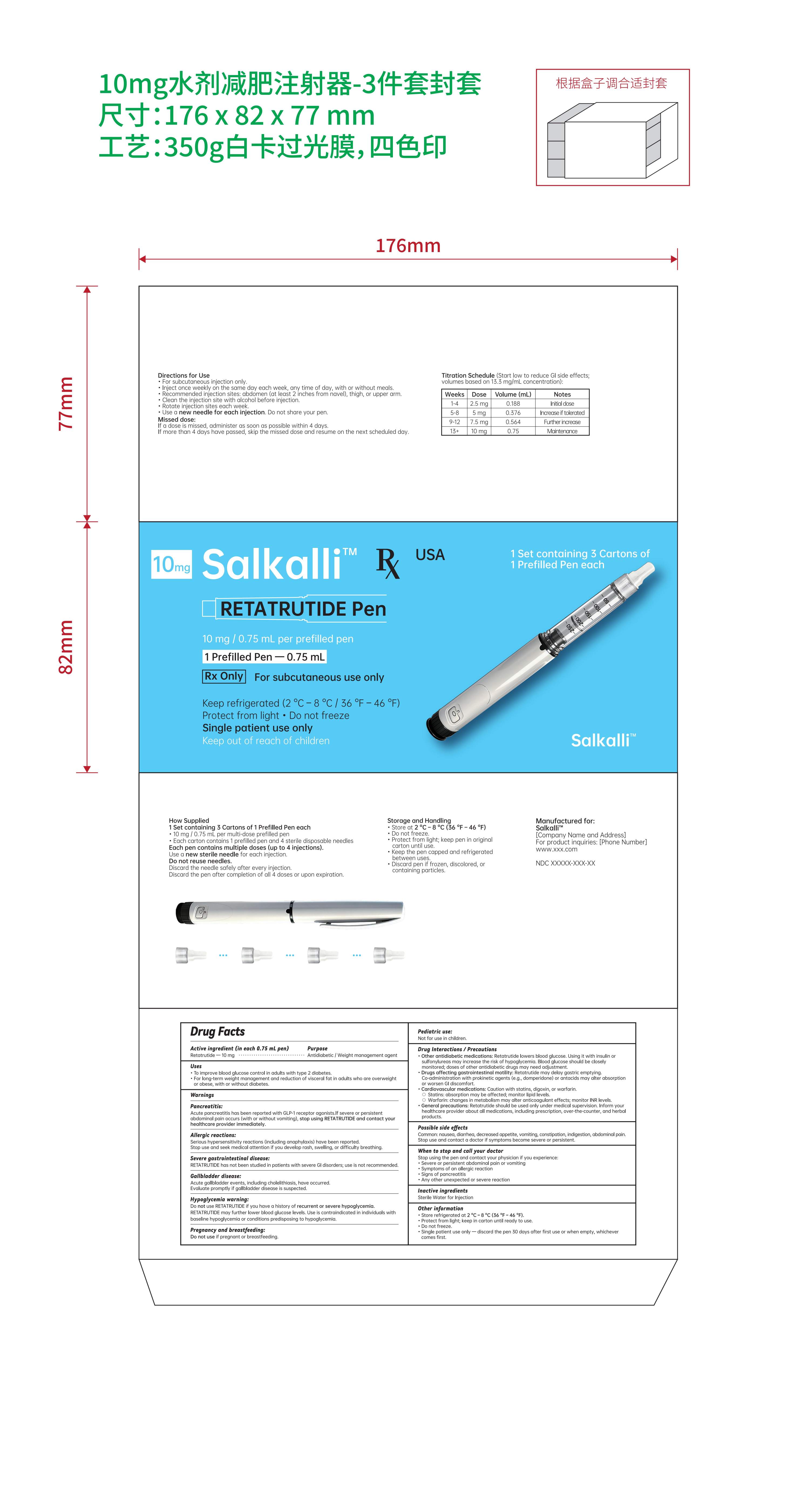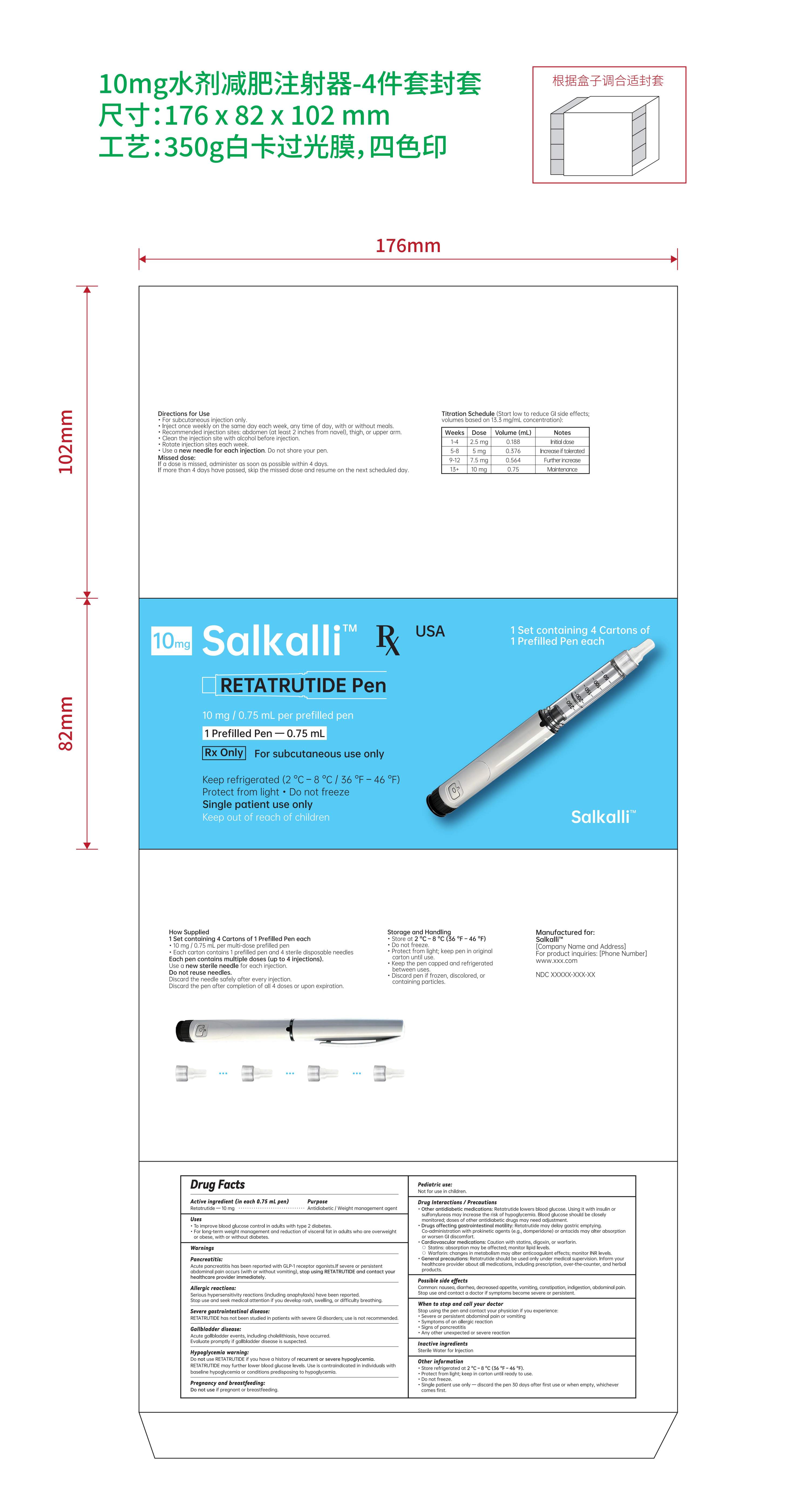 DRUG LABEL: Salkalli
NDC: 84778-111 | Form: INJECTION, SOLUTION
Manufacturer: Guangzhou Yixin Cross-border E-commerce Co., Ltd.
Category: prescription | Type: HUMAN PRESCRIPTION DRUG LABEL
Date: 20251107

ACTIVE INGREDIENTS: RETATRUTIDE 10 mg/1 mL
INACTIVE INGREDIENTS: AQUA

Active ingredient (in each 0.75 mL pen)

Retatrutide — 10 mg

Purpose

Antidiabetic / Weight management agent

Uses

To improve blood glucose control in adults with type 2 diabetes.

For long-term weight management and reduction of visceral fat in adults who are overweight or obese, with or without diabetes.

Warnings

Pancreatitis: Acute pancreatitis has been reported with GLP-1 receptor agonists. If severe or persistent abdominal pain occurs (with or without vomiting), stop using RETATRUTIDE and contact your healthcare provider immediately.

Allergic reactions: Serious hypersensitivity reactions (including anaphylaxis) have been reported.

Stop use and seek medical attention if you develop rash, swelling, or difficulty breathing.

Severe gastrointestinal disease: RETATRUTIDE has not been studied in patients with severe GI disorders; use is not recommended.

Gallbladder disease: Acute gallbladder events, including cholelithiasis, have occurred. Evaluate promptly if gallbladder disease is suspected.

Hypoglycemia warning:

Do not use RETATRUTIDE if you have a history of recurrent or severe hypoglycemia.

RETATRUTIDE may further lower blood glucose levels. Use is contraindicated in individuals with baseline hypoglycemia or conditions predisposing to hypoglycemia.

Pregnancy and breastfeeding: Do not use if pregnant or breastfeeding.

Pediatric use: Not for use in children.

Drug Interactions / Precautions

Other antidiabetic medications: Retatrutide lowers blood glucose. Using it with insulin or sulfonylureas may increase the risk of hypoglycemia. Blood glucose should be closely monitored; doses of other antidiabetic drugs may need adjustment.
Drugs affecting gastrointestinal motility: Retatrutide may delay gastric emptying. Co-administration with prokinetic agents (e.g., domperidone) or antacids may alter absorption or worsen GI discomfort.
Cardiovascular medications: Caution with statins, digoxin, or warfarin.

Statins: absorption may be affected; monitor lipid levels.
Warfarin: changes in metabolism may alter anticoagulant effects; monitor INR levels.

General precautions: Retatrutide should be used only under medical supervision. Inform your healthcare provider about all medications, including prescription, over-the-counter, and herbal products.

Possible side effects

Common: nausea, diarrhea, decreased appetite, vomiting, constipation, indigestion, abdominal pain.

Stop use and contact a doctor if symptoms become severe or persistent.

When to stop and call your doctor

Stop using the pen and contact your physician if you experience:

• Severe or persistent abdominal pain or vomiting

• Symptoms of an allergic reaction

• Signs of pancreatitis

• Any other unexpected or severe reaction

Titration schedule:

Weeks 1–4 0.19 mL (2.5 mg) once weekly

Weeks 5–8 0.37 mL (5 mg) once weekly

Weeks 9–12 0.56 mL (7.5 mg) once weekly

Week 13 and beyond 0.75 mL (10 mg) once weekly

Directions for Use

• For subcutaneous injection only.

• Inject once weekly on the same day each week, any time of day, with or without meals.

• Recommended injection sites: abdomen, thigh, or upper arm.

• Clean the injection site with alcohol before injection.

• Rotate injection sites each week.

• Use a new needle for each injection. Do not share your pen.

Uses

• To improve blood glucose control in adults with type 2 diabetes.

• For long-term weight management and reduction of visceral fat in adults who are overweight or obese, with or without diabetes.

Warnings

Pancreatitis: Acute pancreatitis has been reported with GLP-1 receptor agonists. If severe or persistent abdominal pain occurs (with or without vomiting), stop using RETATRUTIDE and contact your healthcare provider immediately.

Allergic reactions: Serious hypersensitivity reactions (including anaphylaxis) have been reported.

Stop use and seek medical attention if you develop rash, swelling, or difficulty breathing.

Severe gastrointestinal disease: RETATRUTIDE has not been studied in patients with severe GI disorders; use is not recommended.

Gallbladder disease: Acute gallbladder events, including cholelithiasis, have occurred. Evaluate promptly if gallbladder disease is suspected.

Hypoglycemia warning:

Do not use RETATRUTIDE if you have a history of recurrent or severe hypoglycemia.

RETATRUTIDE may further lower blood glucose levels. Use is contraindicated in individuals with baseline hypoglycemia or conditions predisposing to hypoglycemia.

Pregnancy and breastfeeding: Do not use if pregnant or breastfeeding.

Pediatric use: Not for use in children.

Drug Interactions / Precautions

Other antidiabetic medications: Retatrutide lowers blood glucose. Using it with insulin or sulfonylureas may increase the risk of hypoglycemia. Blood glucose should be closely monitored; doses of other antidiabetic drugs may need adjustment.
Drugs affecting gastrointestinal motility: Retatrutide may delay gastric emptying. Co-administration with prokinetic agents (e.g., domperidone) or antacids may alter absorption or worsen GI discomfort.
Cardiovascular medications: Caution with statins, digoxin, or warfarin.

Statins: absorption may be affected; monitor lipid levels.
Warfarin: changes in metabolism may alter anticoagulant effects; monitor INR levels.

General precautions: Retatrutide should be used only under medical supervision. Inform your healthcare provider about all medications, including prescription, over-the-counter, and herbal products.

Possible side effects

Common: nausea, diarrhea, decreased appetite, vomiting, constipation, indigestion, abdominal pain.

Stop use and contact a doctor if symptoms become severe or persistent.

When to stop and call your doctor

Stop using the pen and contact your physician if you experience:

• Severe or persistent abdominal pain or vomiting

• Symptoms of an allergic reaction

• Signs of pancreatitis

• Any other unexpected or severe reaction

stop use

Pancreatitis: Acute pancreatitis has been reported with GLP-1 receptor agonists. If severe or persistent abdominal pain occurs (with or without vomiting), stop using RETATRUTIDE and contact your healthcare provider immediately.

Allergic reactions: Serious hypersensitivity reactions (including anaphylaxis) have been reported.

Stop use and seek medical attention if you develop rash, swelling, or difficulty breathing.

Severe gastrointestinal disease: RETATRUTIDE has not been studied in patients with severe GI disorders; use is not recommended.

Gallbladder disease: Acute gallbladder events, including cholelithiasis, have occurred. Evaluate promptly if gallbladder disease is suspected.

Hypoglycemia warning:

Do not use RETATRUTIDE if you have a history of recurrent or severe hypoglycemia.

RETATRUTIDE may further lower blood glucose levels. Use is contraindicated in individuals with baseline hypoglycemia or conditions predisposing to hypoglycemia.

Pregnancy and breastfeeding: Do not use if pregnant or breastfeeding.

Pediatric use: Not for use in children.

Drug Interactions / Precautions

Other antidiabetic medications: Retatrutide lowers blood glucose. Using it with insulin or sulfonylureas may increase the risk of hypoglycemia. Blood glucose should be closely monitored; doses of other antidiabetic drugs may need adjustment.
Drugs affecting gastrointestinal motility: Retatrutide may delay gastric emptying. Co-administration with prokinetic agents (e.g., domperidone) or antacids may alter absorption or worsen GI discomfort.
Cardiovascular medications: Caution with statins, digoxin, or warfarin.

Statins: absorption may be affected; monitor lipid levels.
Warfarin: changes in metabolism may alter anticoagulant effects; monitor INR levels.

General precautions: Retatrutide should be used only under medical supervision. Inform your healthcare provider about all medications, including prescription, over-the-counter, and herbal products.

Possible side effects

Common: nausea, diarrhea, decreased appetite, vomiting, constipation, indigestion, abdominal pain.

Stop use and contact a doctor if symptoms become severe or persistent.

When to stop and call your doctor

Stop using the pen and contact your physician if you experience:

• Severe or persistent abdominal pain or vomiting

• Symptoms of an allergic reaction

• Signs of pancreatitis

• Any other unexpected or severe reaction

Keep out of reach of children.

Inactive ingredients

Sterile Water for Injection